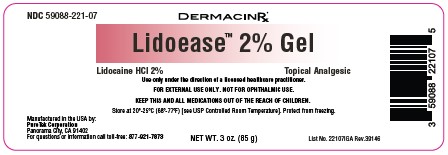 DRUG LABEL: Lidoease 2%
NDC: 59088-221 | Form: GEL
Manufacturer: PureTek Corporation
Category: otc | Type: HUMAN OTC DRUG LABEL
Date: 20250806

ACTIVE INGREDIENTS: LIDOCAINE HYDROCHLORIDE 20 mg/1 g
INACTIVE INGREDIENTS: DIMETHICONE; PROPYLENE GLYCOL; CARBOMER; CUCUMBER; CAPRYLYL GLYCOL; ALOE BARBADENSIS LEAF JUICE; CHLORPHENESIN; GLYCERIN; PROPANEDIOL; SODIUM HYDROXIDE; WATER; PHENOXYETHANOL

NDC 59088-221 Lidoease™ 2% Gel

Active Ingredient

Lidocaine HCl 2%

Purpose

Topical Analgesic

Uses

For the temporarily relief of pain and itching associated with:
■ minor burns ■ sunburn ■ minor cuts ■ scrapes ■ insect bites ■ minor skin irritations

Warnings

For external use only.

When using this product:

■ Avoid contact with the eyes. ■ Do not use in large quantities, particularly over raw surfaces or blistered areas.

Stop use and ask a doctor if

■ If condition worsens, or if symptoms persist for more than 7 days or clear up and occur again within a few days

Keep out of reach of children.

If swallowed, get medical help or contact a Poison Control Center right away.

Directions:

■ Adults and children 2 years or older: Apply externally to the affected area up to 3-4 times daily.
■ Children under 2 years: do not use, consult a doctor.

Other information

■ Store at USP controlled room temperature 20° to 25°C (68° to 77°F)

Inactive ingredients:

Aloe Barbadensis (Aloe Vera) Leaf Juice, Aqua (Purified Water), Caprylyl Glycol, Carbomer, Chlorphenesin, Cucumis Sativus (Cucumber) Fruit Extract, Dimethicone, Glycerin, Phenoxyethanol, Propanediol, Propylene Glycol, Sodium Hydroxide.